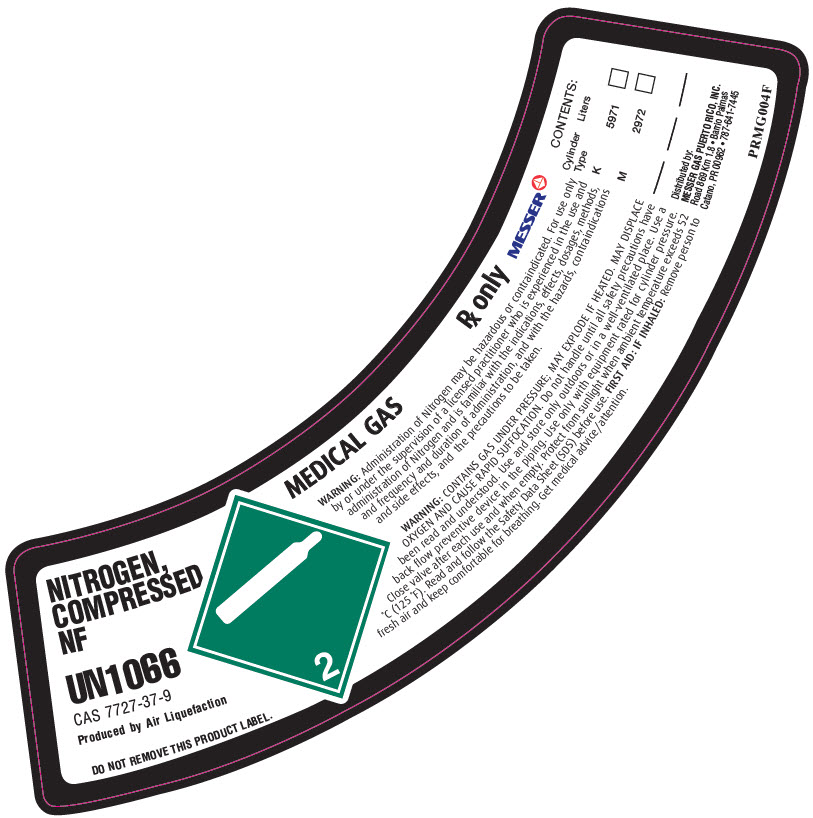 DRUG LABEL: Nitrogen
NDC: 52374-002 | Form: GAS
Manufacturer: Messer Gas Puerto Rico, Inc
Category: prescription | Type: HUMAN PRESCRIPTION DRUG LABEL
Date: 20251118

ACTIVE INGREDIENTS: NITROGEN 99 L/100 L

Messer PR - NITROGEN, COMPRESSED -002

WARNINGS AND PRECAUTIONS SECTION

WARNING:Administration of Nitrogen may be hazardour or contraindicated. For use only by or under the supervision of a licensed practitioner who is experienced in the use and administration of Nitrogen and is familiar with the indications, effects, dosages, methods, and frequency and duration of administration, and with the hazards, contraindications and side effects, and the precautions to be taken.
WARNING:CONTAINS GAS UNDER PRESSURE; MAY EXPLODE IF HEATED. MAY DISPLACE OXYGEN AND CAUSE RAPID SUFFOCATION. Do not handle until all safety precautions have been read and understood. Use and store only outdoors or in a well-ventilated place. Use a back flow preventive device in the piping. Use only with equipment fated for cylinder pressure. Close valve after each use and when empty. Protect from sunlight when ambient temperature exceeds 52°C (125°F). Read and follow the Safety Data Sheet (SDS) before use. FIRST AID: IF INHALED:Remove person to fresh air and keep comfortable for breathing. Get medical advice/attention.

PACKAGE LABEL

NITROGEN, COMPRESSED NF

UN1066

CAS 7727-37-9

Produced by Air Liquefaction

DO NOT REMOVE THIS PRODUCT LABEL.
2

Messer

MEDICAL GAS

Rx only

CONTENTS:
Cylinder Type | Liters
K | 5971 | _____
M | 2972 | _____
_______ | _______ | _____
_______ | _______ | _____
_______ | _______ | _______

Distributed by:
Messer Gas Puerto, Inc.
Road 869 Km 1.8
Catano, PR 00962
787-641-7445

PRMG004F